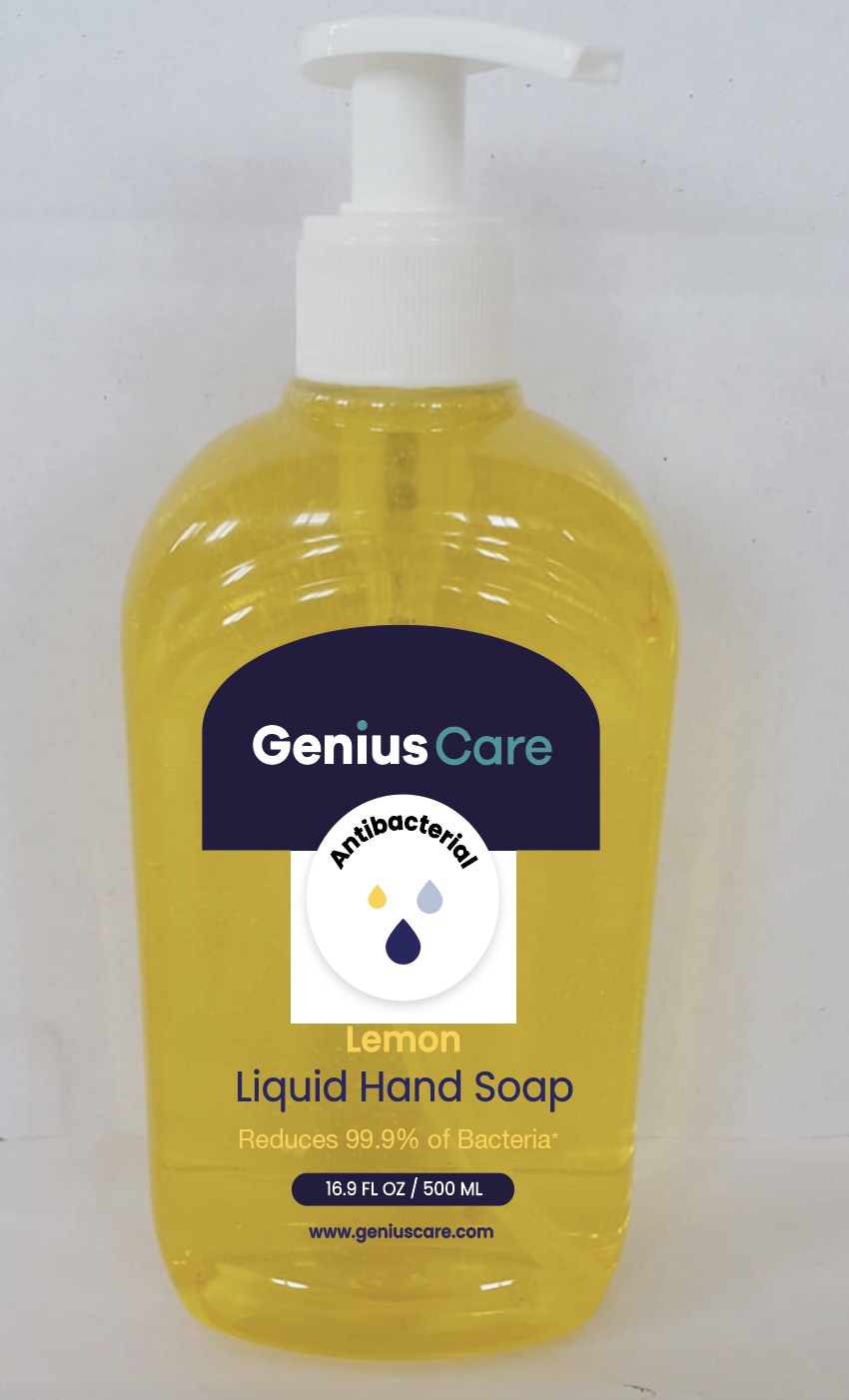 DRUG LABEL: GENIUS CARE ANTIBACTERIAL handsoap LEMON
NDC: 79320-121 | Form: SOAP
Manufacturer: RK KOZMETIK VE HIJYEN URUNLERI SANAYI DIS TICARET ANONIM SIRKETI
Category: otc | Type: HUMAN OTC DRUG LABEL
Date: 20200930

ACTIVE INGREDIENTS: BENZALKONIUM CHLORIDE 1.3 g/1 L
INACTIVE INGREDIENTS: LAURAMINE OXIDE 1 g/1 L; PEG-120 METHYL GLUCOSE DIOLEATE 0.7 g/1 L; SULISOBENZONE 0.05 g/1 L; MAGNESIUM NITRATE 0.05 g/1 L; METHYLCHLOROISOTHIAZOLINONE/METHYLISOTHIAZOLINONE MIXTURE 0.001 g/1 L; GLYCERIN 2 g/1 L; SODIUM CHLORIDE 1.5 g/1 L; WATER; LEMON JUICE 0.1 g/1 L; COCAMIDOPROPYL BETAINE 4 g/1 L; MAGNESIUM CHLORIDE 0.05 g/1 L; CETRIMONIUM CHLORIDE 1.5 g/1 L; COCO MONOETHANOLAMIDE 1.5 g/1 L; FD&C YELLOW NO. 5 0.0004 g/1 L; D&C RED NO. 33 0.0001 g/1 L

Active Ingredient(s)

Benzalconium Choloride 0.13 % Purpose: Antiseptic

Purpose

Antiseptic, Genius Care Antibacterial Hand Soap

Uses

For handwashing to help decrease bacteria on the skin.

Warnings

For external use only.

Keep away from fire.

Dont use in or near the eyes.

in case of contact, rinse eyes thoroughly with water.

Stop use and ask doctor if irritation or redness devolops.

Keep out of rich children.

If swallowed, get medical help or contact a Poison Control Center right away.

When using this product avoid contact with eyes. If contact occurs, rinse thoroughly with water.

Stop use and ask a doctor if irritation or redness devolops and lasts.

Keep out of reach of children. In case of accidental ingestion, get medical help or contact a poison Control Center immediately.

Directions

- Pump into hands. wet as needed.
- Lather vigorously for at least 15 seconds.
- Wash skin, rinse thoroughly and dry.
- Children under 6 years of age should be supervised when using.

Other information

- Store between 110 F (43 C).

Inactive ingredients

Water (Aqua), Cocamidopropyl Betain, Glycerin, Sodium Chloirde, Cocamide MEA, Lauramine Oxide,

PEG-120 Methyl Glucose Dioleate, PArfum, Tetrasodium EDTA, Citric Acid, Benzophenone-4, Citrus Limon (Lemon) Fruit Extract,

Magnesium Chloride, Magnesium Nitrate, Methylchloroisothiazolinone, Methylisothiazolinone, C.I. 19140, C.I. 17200

Package Label - Principal Display Panel

500 mL NDC: 79320-121-01